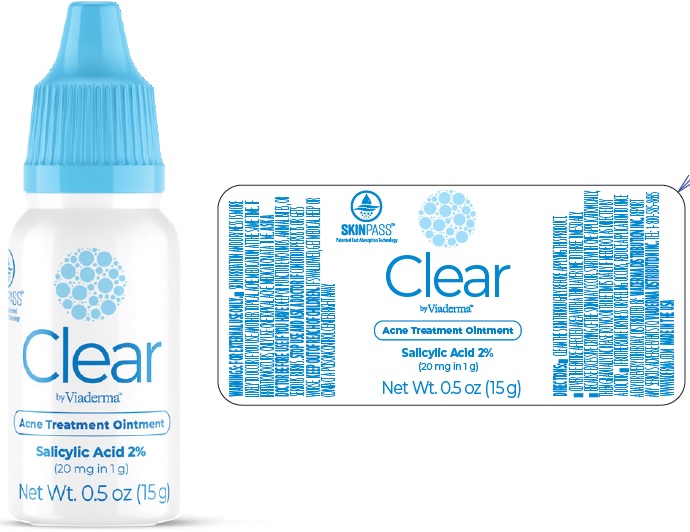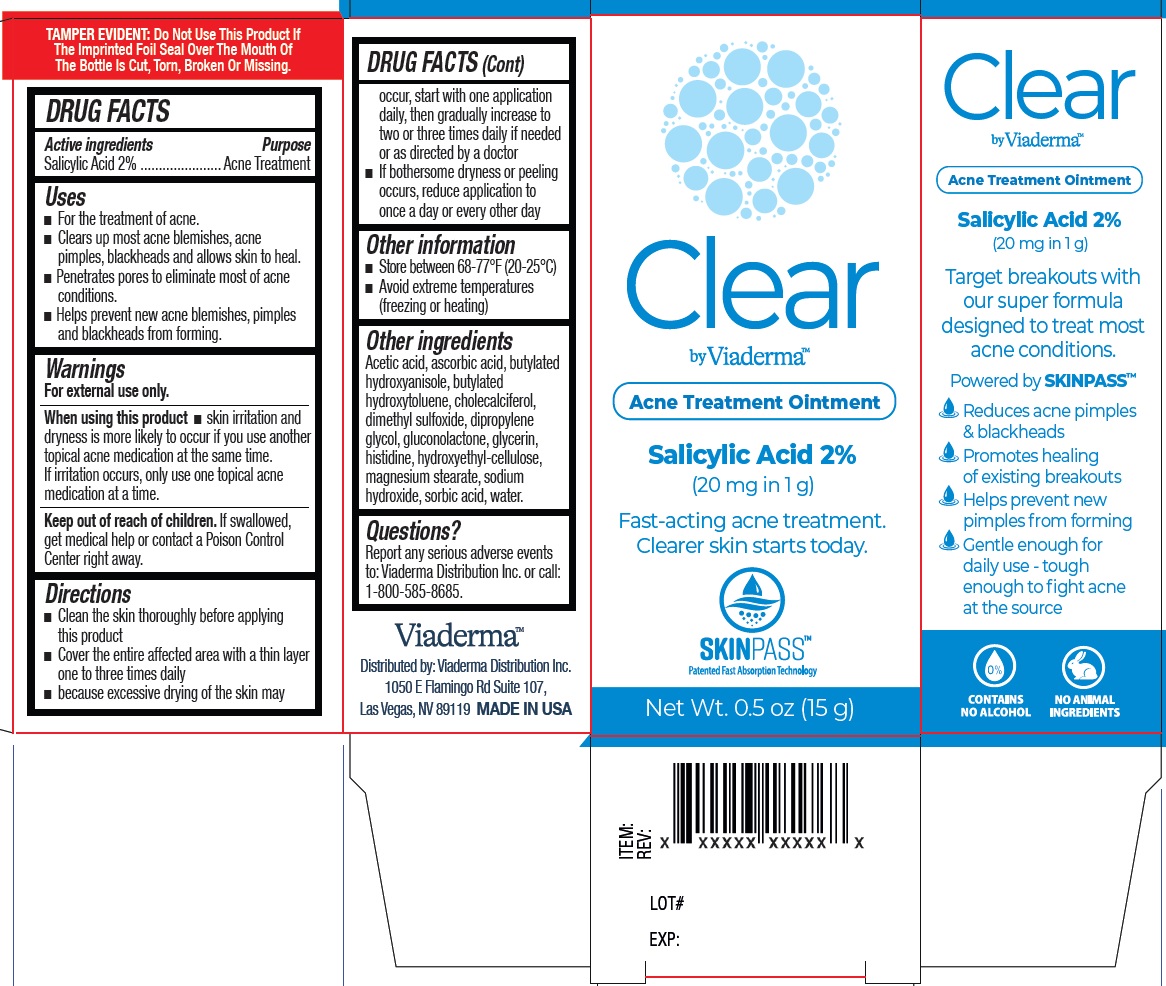 DRUG LABEL: Viaderma Clear Acne Treatment
NDC: 71262-016 | Form: OINTMENT
Manufacturer: ViaDerma Distribution, Inc.
Category: otc | Type: HUMAN OTC DRUG LABEL
Date: 20251002

ACTIVE INGREDIENTS: SALICYLIC ACID 20 mg/1 g
INACTIVE INGREDIENTS: ACETIC ACID; ASCORBIC ACID; BUTYLATED HYDROXYANISOLE; BUTYLATED HYDROXYTOLUENE; CHOLECALCIFEROL; DIMETHYL SULFOXIDE; DIPROPYLENE GLYCOL; GLUCONOLACTONE; GLYCERIN; HISTIDINE; HYDROXYETHYL CELLULOSE, UNSPECIFIED; MAGNESIUM STEARATE; SODIUM HYDROXIDE; SORBIC ACID; WATER

Viaderma Clear Acne Treatment Ointment

Active ingredients

Salicylic Acid 2%

Purposes

Acne Treatment

Uses

- For the treatment of acne.
- Clears up most acne blemishes, acne pimples, blackheads and allows skin to heal.
- Penetrates pores to eliminate most of acne conditions.
- Helps prevent new acne blemishes, pimples and blackheads from forming.

Warnings

For external use only.

When using this product

- skin irritation and dryness is more likely to occur if you use another topical acne medication at the same time. If irritation occurs, only use one topical acne medication at a time.

Keep out of reach of children.

If swallowed, get medical help or contact a Poison Control Center right away.

Directions

- Clean the skin thoroughly before applying this product
- Cover the entire affected area with a thin layer one to three times daily
- because excessive drying of the skin may occur, start with one application daily, then gradually increase to two or three times daily if needed or as directed by a doctor
- If bothersome dryness or peeling occurs, reduce application to once a day or every other day

Other information

- Store between 68-77°F (20-25°C)
- Avoid extreme temperatures (freezing or heating)

Other ingredients

Acetic acid, ascorbic acid, butylated hydroxyanisole, butylated hydroxytoluene, cholecalciferol, dimethyl sulfoxide, dipropylene glycol, gluconolactone, glycerin, histidine, hydroxyethyl-cellulose, magnesium stearate, sodium hydroxide, sorbic acid, water.

Questions?

Report any serious adverse events
to: Viaderma Distribution Inc. or call:
1-800-585-8685.